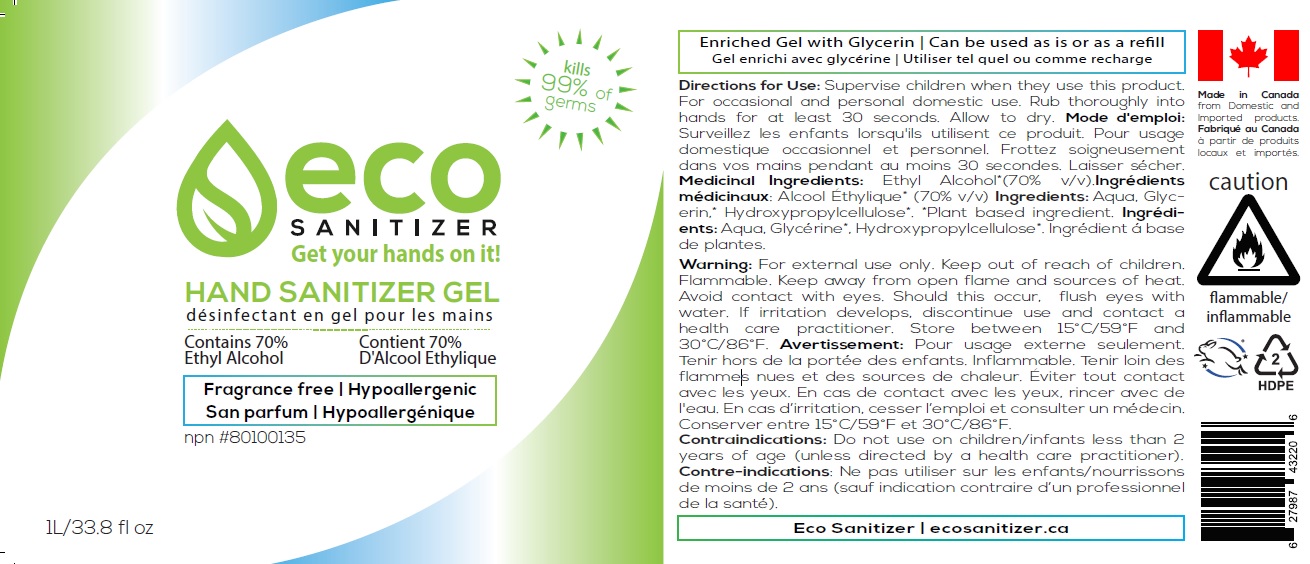 DRUG LABEL: Eco Sanitizer Gel
NDC: 80731-002 | Form: GEL
Manufacturer: 0966452 B.C. Ltd.
Category: otc | Type: HUMAN OTC DRUG LABEL
Date: 20201028

ACTIVE INGREDIENTS: ALCOHOL 70 mL/100 mL
INACTIVE INGREDIENTS: WATER; GLYCERIN; HYDROXYPROPYL CELLULOSE, UNSPECIFIED

eco SANITIZER HAND SANITIZER GEL

Purpose: Antiseptic

INDICATIONS AND USAGE

Use: Hand sanitizer to help reduce bacteria on skin

DOSAGE AND ADMINISTRATION

Directions for Use: Supervise children when they use this product. For occasional and personal domestic use. Rub thoroughly into hands for at least 30 seconds. Allow to dry.

ACTIVE INGREDIENT

Medicinal Ingredients: Ethyl Alcohol* (70% v/v).

INACTIVE INGREDIENT

Ingredients: Aqua, Glycerin,* Hydroxypropylcellulose*. *Plant based ingredient.

WARNINGS

Warning: For external use only. Keep out of reach of children. Flammable. Keep away from open flame and sources of heat. Avoid contact with eyes. Should this occur, flush eyes with water. If irritation develops, discontinue use and contact a health care practitioner. Store between 15°C/59°F and 30°C/86°F.

Contraindications: Do not use on children/infants less than 2 years of age (unless directed by a health care practitioner).

Keep out of reach of children.

kills 99% of germs

Get your hands on it!

Fragrance free | Hypoallergenic

Enriched Gel with Glycerin | Can be used as is or as a refill

Made in Canada from Domestic and Imported products.

Eco Sanitizer | ecosanitizer.ca